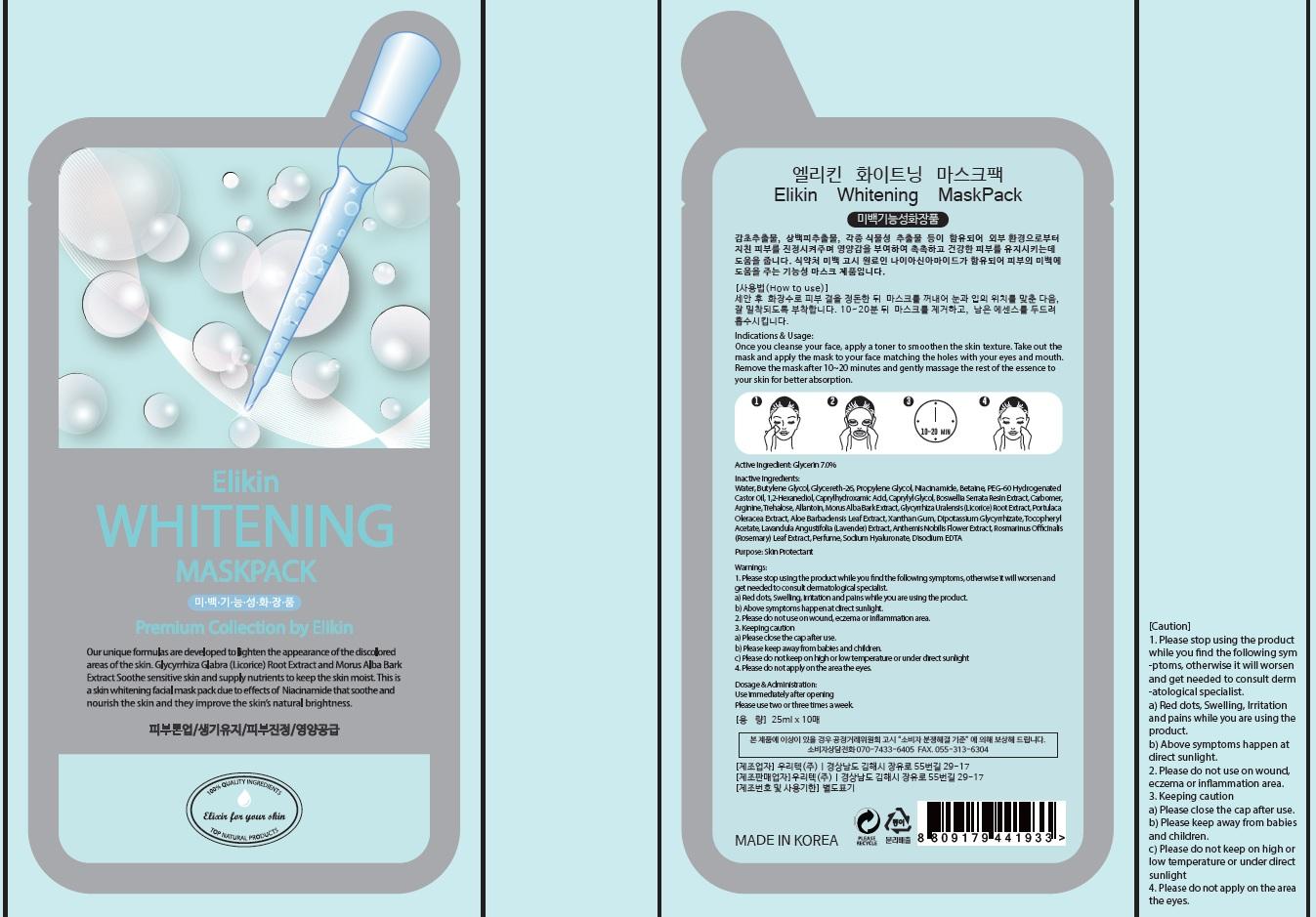 DRUG LABEL: Elikin Whitening MaskPack
NDC: 70221-050 | Form: PATCH
Manufacturer: WOORITECH CO., LTD
Category: otc | Type: HUMAN OTC DRUG LABEL
Date: 20151117

ACTIVE INGREDIENTS: Glycerin 1.75 mg/10 1
INACTIVE INGREDIENTS: Water; Butylene Glycol

ACTIVE INGREDIENT

Active Ingredient: Glycerin 7.0%

INACTIVE INGREDIENT

Inactive Ingredients: Water, Butylene Glycol, Glycereth-26, Propylene Glycol, Niacinamide, Betaine, PEG-60 Hydrogenated Castor Oil, 1,2-Hexanediol, Caprylhydroxamic Acid, Caprylyl Glycol, Boswellia Serrata Resin Extract, Carbomer, Arginine, Trehalose, Allantoin, Morus Alba Bark Extract, Glycyrrhiza Uralensis (Licorice) Root Extract, Portulaca Oleracea Extract, Aloe Barbadensis Leaf Extract, Xanthan Gum, Dipotassium Glycyrrhizate, Tocopheryl Acetate, Lavandula Angustifolia (Lavender) Extract, Anthemis Nobilis Flower Extract, Rosmarinus Officinalis (Rosemary) Leaf Extract, Perfume, Sodium Hyaluronate, Disodium EDTA

PURPOSE

Purpose: Skin Protectant

WARNINGS

Warnings: 1. Please stop using the product while you find the following symptoms, otherwise it will worsen and get needed to consult dermatological specialist. a) Red dots, Swelling, Irritation and pains while you are using the product. b) Above symptoms happen at direct sunlight. 2. Please do not use on wound, eczema or inflammation area. 3. Keeping caution a) Please close the cap after use. b) Please keep away from babies and children. c) Please do not keep on high or low temperature or under direct sunlight 4. Please do not apply on the area the eyes.

KEEP OUT OF REACH OF CHILDREN

Please keep away from babies and children.

INDICATIONS & USAGE

Indications & Usage: Once you cleanse your face, apply a toner to smoothen the skin texture. Take out the mask and apply the mask to your face matching the holes with your eyes and mouth. Remove the mask after 10~20 minutes and gently massage the rest of the essence to your skin for better absorption.

DOSAGE & ADMINISTRATION

Dosage & Administration: Use immediately after opening Please use two or three times a week.